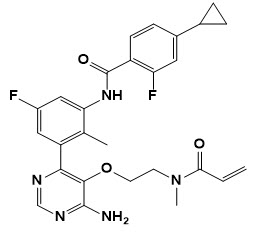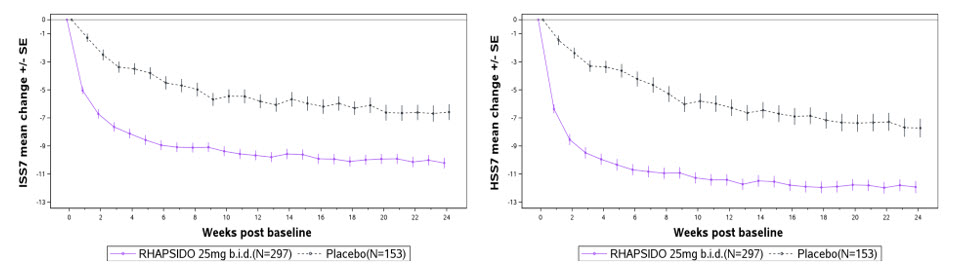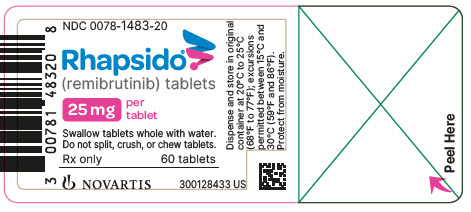 DRUG LABEL: RHAPSIDO
NDC: 0078-1483 | Form: TABLET
Manufacturer: Novartis Pharmaceuticals Corporation
Category: prescription | Type: HUMAN PRESCRIPTION DRUG LABEL
Date: 20250930

ACTIVE INGREDIENTS: REMIBRUTINIB 25 mg/1 1
INACTIVE INGREDIENTS: COPOVIDONE K25-31; CROSCARMELLOSE SODIUM; MANNITOL; MICROCRYSTALLINE CELLULOSE; SODIUM LAURYL SULFATE; SODIUM STEARYL FUMARATE; POLYETHYLENE GLYCOL 4000; POLYVINYL ALCOHOL, UNSPECIFIED; FERRIC OXIDE RED; TALC; TITANIUM DIOXIDE; FERRIC OXIDE YELLOW

HIGHLIGHTS OF PRESCRIBING INFORMATION

These highlights do not include all the information needed to use RHAPSIDO safely and effectively. See full prescribing information for RHAPSIDO.
RHAPSIDO® (remibrutinib) tablets, for oral use
Initial U.S. Approval: 2025

1 INDICATIONS AND USAGE

RHAPSIDO® is a kinase inhibitor indicated for the treatment of chronic spontaneous urticaria (CSU) in adult patients who remain symptomatic despite H1 antihistamine treatment. (1)

Limitations of Use: Not indicated for other forms of urticaria. (1)

2 DOSAGE AND ADMINISTRATION

Recommended dosage is 25 mg orally twice daily with or without food. (2.1)

- Swallow tablets whole. Do not split, crush, or chew RHAPSIDO. (2.1)
- Interrupt RHAPSIDO for 3 to 7 days pre- and post-surgery. (2.2)

3 DOSAGE FORMS AND STRENGTHS

Tablets: 25 mg (3)

4 CONTRAINDICATIONS

None. (4)

5 WARNINGS AND PRECAUTIONS

- Risk of Bleeding: Monitor for signs and symptoms of bleeding. Interrupt treatment with RHAPSIDO if bleeding is observed or pre- and post-surgery. Concomitant use of antithrombotic agents with RHAPSIDO may further increase risk of bleeding. (5.1)
- Live Attenuated Vaccines: Avoid live or live-attenuated vaccines in patients receiving RHAPSIDO. (5.2)

6 ADVERSE REACTIONS

The most common adverse reactions (incidence ≥3%) were nasopharyngitis, bleeding, headache, nausea and abdominal pain. (6.1)

To report SUSPECTED ADVERSE REACTIONS, contact Novartis Pharmaceuticals Corporation at 1-888-669-6682 or FDA at 1-800-FDA-1088 or www.fda.gov/medwatch.

7 DRUG INTERACTIONS

- Strong or Moderate CYP3A4 Inhibitors: Avoid concomitant use with RHAPSIDO. (7.1)
- Strong or Moderate CYP3A4 Inducers: Avoid concomitant use with RHAPSIDO. (7.1)
- P-gp Substrates: Exposure increases where minimal concentration changes may lead to serious adverse reactions: Monitor more frequently for adverse reactions when used concomitantly with RHAPSIDO. (7.2)
- Antithrombotic Agents: Consider the risks and benefits of concomitant use of antithrombotic agents with RHAPSIDO. (7.2)

8 USE IN SPECIFIC POPULATIONS

- Mild, Moderate, or Severe Hepatic Impairment: Avoid use of RHAPSIDO. (8.6)

FULL PRESCRIBING INFORMATION

1 INDICATIONS AND USAGE

RHAPSIDO® is indicated for the treatment of chronic spontaneous urticaria (CSU) in adult patients who remain symptomatic despite H1 antihistamine treatment.

Limitations of Use:

RHAPSIDO is not indicated for other forms of urticaria.

2 DOSAGE AND ADMINISTRATION

2.1 Recommended Dosage

The recommended dosage is 25 mg taken orally twice daily with or without food.

- Swallow RHAPSIDO tablet whole with water. Do not split, crush, or chew RHAPSIDO.

Missed Dose(s)

If a dose or doses of RHAPSIDO is missed, skip the missed dose, and take the next dose at its regularly scheduled time. Do not take an extra dose(s) of RHAPSIDO to make up for a missed dose(s).

2.2 Temporary Interruption of RHAPSIDO for Surgery

Interrupt treatment with RHAPSIDO for 3 to 7 days pre- and post-surgery depending upon the type of surgery and the risk of bleeding [see Warnings and Precautions (5.1), Adverse Reactions (6.1) and Drug Interactions (7.2)].

3 DOSAGE FORMS AND STRENGTHS

Tablets: 25 mg, light yellow, round, curved, unscored, film-coated tablet, debossed with “LV” on one side and Novartis logo on the other side. The tablet diameter is 7 mm.

4 CONTRAINDICATIONS

None.

5 WARNINGS AND PRECAUTIONS

5.1 Risk of Bleeding

In placebo-controlled studies in patients with CSU, mucocutaneous-related bleeding occurred in 9% of patients who received RHAPSIDO [see Adverse Reactions (6.1)]. Interrupt treatment with RHAPSIDO if bleeding is observed and resume if the benefit is expected to outweigh the risk.

Interrupt treatment with RHAPSIDO for 3 to 7 days pre- and post-surgery or invasive procedures [see Dosage and Administration (2.2)].

Use of antithrombotic agents concomitantly with RHAPSIDO may further increase the risk of bleeding [see Drug Interactions (7.2)]. Consider the benefits and risks of antithrombotic agents when used concomitantly with RHAPSIDO. Monitor for signs and symptoms of bleeding.

5.2 Live Attenuated Vaccines

No data are available on the effects of live or live-attenuated vaccines in patients receiving RHAPSIDO. The use of live and live-attenuated vaccines should be avoided in patients receiving RHAPSIDO.

6 ADVERSE REACTIONS

6.1 Clinical Trials Experience

Because clinical trials are conducted under widely varying conditions, adverse drug reaction (ADR) rates observed in the clinical trials of a drug cannot be directly compared to rates in the clinical trials of another drug and may not reflect the rates observed in practice.

The safety of RHAPSIDO was based on a pooled safety population from two identical clinical trials of 52 weeks duration, REMIX-1 and REMIX-2 [see Clinical Studies (14)]. The pooled safety population consisted of 912 adult patients with CSU who remain symptomatic despite H1 antihistamine treatment and who received RHAPSIDO 25 mg orally twice daily (N=606) or placebo (N=306) for 24 weeks during the double-blind, controlled treatment period of the trial.

Adverse reactions that occurred at an incidence greater than or equal to 3% and more common than the placebo group from the pooled safety population (REMIX-1 and REMIX-2) during the 24-week blinded, placebo-controlled treatment period are shown in Table 1.

Table 1 Adverse Reactions with RHAPSIDO with Incidence ≥3% and More Common than Placebo in Adult Patients with CSU (REMIX-1 and REMIX-2)
Adverse Reaction | RHAPSIDO (N = 606) n (%) | Placebo (N = 306) n (%)
Nasopharyngitisa | 67 (11%) | 27 (9%)
Bleedingb | 55 (9%) | 6 (2%)
Headachec | 41 (7%) | 19 (6%)
Nausea | 18 (3%) | 5 (2%)
Abdominal Paind | 18 (3%) | 6 (2%)
a includes acute sinusitis, chronic sinusitis, nasopharyngitis, pharyngitis, pharyngitis streptococcal, rhinitis, rhinitis allergic, and upper respiratory tract infection
b includes conjunctival bleeding, contusion, ecchymosis, epistaxis, gingival bleeding, hematoma, hematuria, hemorrhagic ovarian cyst, intermenstrual bleeding, petechiae, purpura, and urinary occult blood
c includes headache and migraine
d includes abdominal discomfort, abdominal distention, abdominal pain and abdominal pain upper

Specific Adverse Reactions

Bleeding

In the pooled safety population (REMIX-1 and REMIX-2), bleeding occurred in 9% of patients treated with RHAPSIDO compared to 2% in the placebo group during the 24-week controlled treatment period [see Dosage and Administration (2.2), Warnings and Precautions (5.1), and Drug Interactions (7.2)]. Petechiae (4%) and contusion (2%) were the most commonly reported reactions in patients treated with RHAPSIDO. No severe bleeding reactions occurred. No association between bleeding reactions and low platelet counts was observed. In patients treated with RHAPSIDO, 0.5% experienced bleeding reactions that led to RHAPSIDO discontinuation, while none of these reactions occurred in the placebo group. Similar safety findings were observed through Week 52 [see Clinical Studies (14)].

7 DRUG INTERACTIONS

7.1 Effect of Other Drugs on RHAPSIDO

Strong or Moderate CYP3A4 Inhibitors

Avoid use of RHAPSIDO with strong or moderate CYP3A4 inhibitors.

Remibrutinib is a CYP3A4 substrate. Concomitant use with a strong or moderate CYP3A4 inhibitor increases remibrutinib exposure [see Clinical Pharmacology (12.3)], which may increase the risk of RHAPSIDO adverse reactions.

Strong or Moderate CYP3A4 Inducers

Avoid use of RHAPSIDO with strong or moderate CYP3A4 inducers.

Remibrutinib is a CYP3A4 substrate. Concomitant use with a strong or moderate CYP3A4 inducer decreases remibrutinib exposure [see Clinical Pharmacology (12.3)], which may decrease the efficacy of RHAPSIDO.

7.2 Effect of RHAPSIDO on Other Drugs

P-gp Substrates

Monitor more frequently for adverse reactions when using RHAPSIDO with P-glycoprotein (P-gp) substrates where minimal concentration changes may lead to serious adverse reactions (e.g., digoxin).

Remibrutinib is a P-gp inhibitor. Remibrutinib increases exposure of P-gp substrates, which may increase the risk of adverse reactions related to P-gp substrates [see Clinical Pharmacology (12.3)].

Antithrombotic Agents

Consider the risks and benefits of concomitant administration of antithrombotic agents with RHAPSIDO [see Dosage and Administration (2.2), Warnings and Precautions (5.1), and Adverse Reactions (6.1)].

No data are available on concomitant use of RHAPSIDO with anticoagulants. The concomitant use of RHAPSIDO and anticoagulants was not allowed in clinical studies. Use of the antiplatelet agents, acetyl salicylic acid at doses up to 100 mg daily or clopidogrel up to 75 mg daily, was allowed in the RHAPSIDO clinical studies.

8 USE IN SPECIFIC POPULATIONS

8.1 Pregnancy

Pregnancy Exposure Registry

There is a pregnancy exposure registry that monitors pregnancy outcomes in women exposed to RHAPSIDO during pregnancy. Pregnant women exposed to RHAPSIDO and healthcare providers are encouraged to contact Novartis Pharmaceuticals Corporation at 1-888-669-6682.

Risk Summary

Available data on the use of RHAPSIDO during pregnancy are insufficient to evaluate for a drug-associated risk of major birth defects, miscarriage or other adverse maternal or fetal outcomes.

In animal reproduction studies, oral administration of remibrutinib to pregnant rabbits during organogenesis at exposures 141-times the human exposure at the maximum recommended human dose (MRHD) of 25 mg twice daily based on area under the curve (AUC) resulted in adverse developmental outcomes including external malformations. No adverse developmental effects were observed with oral administration of remibrutinib to pregnant rats during organogenesis at exposures up to 126-times the human exposure at the MRHD (see Data).

The background risk of major birth defects and miscarriage for the indicated population is unknown. All pregnancies have a background risk of birth defect, loss, or other adverse outcomes. In the U.S. general population, the estimated background risk of major birth defects and miscarriage in clinically recognized pregnancies is 2% to 4% and 15% to 20%, respectively.

Data

Animal Data

In an embryo-fetal development (EFD) study in pregnant rabbits, remibrutinib was administered orally at doses of 100, 300, and 450 mg/kg/day during the period of organogenesis. Increased fetal external malformations (e.g. open/opaque eyes, small jaws, hyperflexion of forelimbs) and maternal toxicity (transiently reduced food consumption and adverse clinical signs) occurred at 300 mg/kg/day (141-times the MRHD based on AUC). The fetal findings were considered unlikely to be secondary to the maternal toxicity. The dose of 450 mg/kg/day was not tolerated by the pregnant rabbits.

In an EFD study in pregnant rats, remibrutinib was administered orally at doses of 100, 300, and 1000 mg/kg/day during the period of organogenesis. Remibrutinib did not cause adverse effects to the fetus at exposures up to 126 times that at the MRHD based on AUC.

In a pre- and postnatal development (PPND) study, remibrutinib was administered orally to pregnant rats at doses of 100, 300, and 1000 mg/kg/day from gestation day 6 to lactation day (LD) 21. Remibrutinib induced adverse effects at 1000 mg/kg/day (approximately 194 times the MRHD based on body surface area [BSA]), affected maternal animals (moribundity and clinical signs of toxicity, slightly longer gestation lengths) and offspring up to LD1 (slightly higher mean number of stillborn, dead, or missing pups, and smaller mean litter size). No adverse effects at doses up to 1000 mg/kg/day were noted in the surviving offspring developing into adulthood. No effects were observed at 300 mg/kg/day (approximately 58 times the MRHD based on BSA).

8.2 Lactation

Risk Summary

No data are available regarding the presence of remibrutinib in either human or animal milk, its effects on the breastfed child, or on milk production. The developmental and health benefits of breastfeeding should be considered along with the mother’s clinical need for RHAPSIDO and any potential adverse effects on the breastfed child from RHAPSIDO or from the underlying maternal condition.

8.4 Pediatric Use

The safety and effectiveness of RHAPSIDO have not been established in pediatric patients.

8.5 Geriatric Use

Of the total number of patients treated with RHAPSIDO in clinical studies for CSU, 53 (8.7%) were 65 to 85 years of age, with no patients over 85 years of age [see Clinical Studies (14)]. There were no observed differences in safety and/or effectiveness in geriatric patients compared to younger adult patients.

8.6 Hepatic Impairment

RHAPSIDO exposure is increased in patients with mild, moderate, or severe hepatic impairment (Child-Pugh Class A, B, and C) relative to patients with normal hepatic function. Avoid use of RHAPSIDO in patients with mild, moderate or severe hepatic impairment (Child-Pugh Class A, B, and C) [see Clinical Pharmacology (12.3)].

10 OVERDOSAGE

Consider contacting the poison help line (1-800-222-1222) or a medical toxicologist for overdose management recommendations.

11 DESCRIPTION

RHAPSIDO (remibrutinib) is a kinase inhibitor.

Its empirical formula (remibrutinib) is C27H27F2N5O3. The chemical name for remibrutinib is N-(3-{6-Amino-5-[2-(N-methylprop-2-enamido)ethoxy]pyrimidin-4-yl}-5-fluoro-2-methylphenyl)-4-cyclopropyl-2-fluorobenzamide. Its molecular weight is approximately 507.54 g/mol. The chemical structure of remibrutinib is:

Remibrutinib is white to pale yellow powder, and it is practically insoluble in water.

RHAPSIDO is supplied as film-coated tablets for oral administration, with each film-coated tablet containing 25 mg of remibrutinib. The tablet core inactive ingredients are copovidone, croscarmellose sodium, mannitol, microcrystalline cellulose, sodium lauryl sulfate, and sodium stearyl fumarate. The tablet coating inactive ingredients are polyethylene glycol 4000, polyvinyl alcohol, red iron oxide (E172), talc, titanium dioxide (E171), and yellow iron oxide (E172).

12 CLINICAL PHARMACOLOGY

12.1 Mechanism of Action

Remibrutinib is an oral, small molecule kinase inhibitor that inhibits Bruton’s tyrosine kinase (BTK). BTK is an intracellular protein expressed in mast cells, basophils, B cells, macrophages, and thrombocytes. BTK is involved in intracellular signaling via Fc epsilon receptor-1 (FcεR1), Fc gamma receptors (FcγR), and the B cell antigen receptor (BCR). Remibrutinib also inhibits the BTK-related kinases tec protein tyrosine kinase (TEC) and BMX non-receptor tyrosine kinase (BMX).

Remibrutinib inhibits mast cell and basophil degranulation, including release of histamine and other proinflammatory mediators, mediated by pathogenic IgE or IgG directed against the FcεR1 or IgE.

12.2 Pharmacodynamics

Exposure-Response

Within the range from 0.2 to 4 times the daily recommended dose, a flat dose-response relationship was observed for the weekly urticaria activity score (UAS7) at Week 4.

Cardiac Electrophysiology

At concentrations approximately 9 times the mean steady state peak plasma concentrations provided by the recommended dose, clinically significant QTc prolongation was not observed.

Effects on Blood Pressure

The effect of remibrutinib treatment on blood pressure was assessed in CSU patients using a 24-hour blood pressure measurement by ambulatory blood pressure monitoring (ABPM) at steady state (Week 4) compared to baseline in a multi-center, open-label study (A2305). The study enrolled 144 patients with CSU inadequately controlled by H1 antihistamines, who were administered remibrutinib 25 mg twice daily. Remibrutinib 25 mg twice daily was not associated with clinically significant changes in blood pressure.

12.3 Pharmacokinetics

Following administration of remibrutinib 25 mg twice daily, the mean (standard deviation) Cmax is 57 (27) ng/mL and AUClast is 193 (136) ng*h/mL at steady state. Remibrutinib Cmax and AUC increase in a dose-proportional manner between 0.4 to 4 times the recommended dosage. Following administration of multiple doses of 25 mg twice daily, Cmax increases 1.6-fold and AUC0-4 increases 2.7-fold.

No clinically significant differences in remibrutinib pharmacokinetics were observed between healthy subjects and patients with CSU.

Absorption

Remibrutinib median (min, max) time to maximum plasma concentration (Tmax) is 1 hour (0, 4 hours) at steady state.

Effect of food

No clinically significant differences in remibrutinib pharmacokinetics were observed following administration of a high-fat meal (1000 calories, 50% fat).

Distribution

Remibrutinib blood-to-plasma ratio is 0.813 in vitro. Plasma protein binding is 95.4% and is not concentration-dependent in vitro. The estimated remibrutinib steady state apparent (oral) volume of distribution is 1238 L.

Elimination

Remibrutinib estimated elimination half-life is 1 to 2 hours with an apparent (oral) clearance of 160 L/hr.

Metabolism

Remibrutinib is primarily metabolized by CYP3A4.

Excretion

Following IV administration of ^14C remibrutinib to healthy subjects, 70% of the total radioactivity was recovered in feces (0% as unchanged remibrutinib), and 30% was recovered in urine (2.9% as unchanged remibrutinib).

Specific Populations

No clinically significant differences in the pharmacokinetics of remibrutinib were observed based on age (range: 18 to 80 years), sex (63.5% females and 36.5% males), race/ethnicity (59.3% Non-Asian [White, Black, and Others], 8.8% Mainland Chinese, 12.2% Japanese, and 19.7% other Asian), body weight (range: 39 to 162 kg), and mild (eGFR 60-89 mL/min/1.73 m^2, estimated by Cockcroft-Gault), moderate (eGFR 30-59 mL/min/1.73 m^2) or severe (eGFR 15-29 mL/min/1.73 m^2) renal impairment.

Patients with Hepatic Impairment

The pharmacokinetics of remibrutinib were evaluated in subjects with mild (Child-Pugh Class A), moderate (Child-Pugh Class B), and severe (Child-Pugh Class C) hepatic impairment following administration of 25 mg twice daily. Relative to patients with normal hepatic function, remibrutinib AUC increased 2.33-fold and Cmax increased 1.85-fold in patients with mild hepatic impairment, AUC increased 2.3-fold and Cmax increased 1.65-fold in patients with moderate hepatic impairment, and AUC increased 3.49-fold and Cmax increased 1.99-fold in patients with severe hepatic impairment [see Use in Special Populations (8.6)].

Drug Interaction Studies

Clinical Studies and Model-Informed Approaches

Strong CYP3A4 Inhibitors: Remibrutinib Cmax increased by 3.3-fold and AUC increased by 4.3-fold following concomitant administration with ritonavir (a strong CYP3A4 inhibitor) 100 mg twice daily for 4 days [see Drug Interactions (7.1)].

Remibrutinib Cmax increased by 1.24-fold and AUC increased by 1.3-fold when co-administered with grapefruit juice.

Moderate CYP3A4 Inhibitors: Remibrutinib Cmax is predicted to increase by approximately 1.9-fold and AUC is predicted to increase by approximately 2.3-fold following concomitant administration with erythromycin (a moderate CYP3A4 inhibitor) 500 mg four times a day for 7 days [see Drug Interactions (7.1)].

Strong CYP3A4 Inducers: Remibrutinib Cmax decreased by 74% and AUC decreased by approximately 77% following concomitant administration with carbamazepine (a strong CYP3A4 inducer) 300 mg twice daily for 14 days [see Drug Interactions (7.1)].

Moderate CYP3A4 Inducers: Remibrutinib Cmax is predicted to decrease by approximately 60% and AUC is predicted to decrease by approximately 64% following concomitant administration with efavirenz (a moderate CYP3A4 inducer) 600 mg once daily for 14 days [see Drug Interactions (7.1)].

P-gp Substrates: Co-administration of remibrutinib at four times the recommended dosage with a single dose of 0.25 mg digoxin (a P-gp substrate) increased digoxin Cmax by 2.1-fold and AUC by 1.4-fold [see Drug Interactions (7.1)].

BCRP Substrates: Co-administration of remibrutinib at four times the recommended dosage with a single dose of 10 mg rosuvastatin (a BCRP and OATP1B substrate) increased rosuvastatin Cmax by 1.6-fold and AUC by 1.7-fold.

Other Drugs: No clinically significant differences in the pharmacokinetics of the following drugs were observed when used concomitantly with remibrutinib: oral midazolam (CYP3A4 substrate), oral contraceptives containing ethinyl estradiol and levonorgestrel (CYP3A4 substrate), tolbutamide (CYP2C9 substrate), caffeine (CYP1A2 substrate), and coproporphyrin I (an endogenous OATP1B substrate).

In Vitro Studies

CYP450 Enzymes: Remibrutinib is a CYP3A4 substrate. Remibrutinib inhibits CYP1A2, CYP2B6, CYP2C8, CYP2C9, CYP2C19, CYP2D6 and CYP3A4/5. Remibrutinib induces CYP1A2, CYP2B6, CYP2C9 and CYP3A4/5.

Transporter Systems: In vitro, remibrutinib is a P-gp substrate. Remibrutinib inhibits P-gp, BCRP, BSEP, OATP1B1, OATP1B3, OAT1, OAT3, OCT1, OCT2 and MATE1.

13 NONCLINICAL TOXICOLOGY

13.1 Carcinogenesis, Mutagenesis, Impairment of Fertility

Remibrutinib did not show evidence of carcinogenic potential in a 6-month rasH2 mouse study at oral doses up to 1500 mg/kg/day and a 2-year rat carcinogenicity study at oral doses up to 300 mg/kg/day (approximately 8 times and 98 times than MRHD of 25 mg twice daily based on AUC for males and females, respectively).

Remibrutinib was not mutagenic in a bacterial mutagenicity (Ames) assay and was not clastogenic in an in vitro micronucleus assay in human peripheral lymphocytes or in an in vivo blood reticulocyte micronucleus assay in rats.

In a fertility study in rats, remibrutinib did not impact fertility in female or male rats up to the maximum achievable exposures of 79 and 15 times higher than MRHD of 25 mg twice daily based on AUC.

14 CLINICAL STUDIES

The efficacy of RHAPSIDO for chronic spontaneous urticaria (CSU) in adult patients who remain symptomatic despite H1 antihistamine treatment was evaluated in two identical, 52-week, multi-center, randomized, double-blind, placebo-controlled clinical trials (REMIX-1 [NCT05030311] and REMIX-2 [NCT05032157]).

REMIX-1 and REMIX-2 enrolled a total of 925 adult patients, diagnosed with CSU inadequately controlled despite treatment with H1 antihistamines, as defined by the presence of itch and hives for ≥6 consecutive weeks. All patients were required to have a weekly urticaria activity score (UAS7) ≥16 (range 0-42), a weekly itch severity score (ISS7) ≥6 (range 0-21) and a weekly hives severity score (HSS7) ≥6 (range 0-21) for 7 days prior to randomization. Patients were randomized in a 2:1 ratio to receive either RHAPSIDO 25 mg or placebo, respectively, orally twice daily for 24 weeks during the double-blind treatment period and subsequently continued in a 28-week open-label treatment period, during which all patients received RHAPSIDO 25 mg twice daily. While REMIX-1 and REMIX-2 clinical trials included an open-label period, efficacy is based on results from 912 patients treated during the controlled period of 24 weeks.

Demographics and baseline characteristics in REMIX-1 and REMIX-2 are provided in Table 2.

Table 2 Baseline Demographic and Disease Characteristics of Adult Patients with CSU in REMIX-1 and REMIX-2
 | REMIX-1 (N=462) | REMIX-2 (N=450)
Age
18-65 years, n (%) | 419 (91) | 416 (92)
>65 years, n (%) | 43 (9) | 34 (8)
Mean age, years | 45 | 42
Sex, n (%)
Female | 313 (68) | 294 (65)
Race, n (%)
White or Caucasian | 270 (58) | 234 (52)
Black or African American | 15 (3) | 10 (2)
Asian | 139 (30) | 201 (45)
Ethnicity, n (%)
Hispanic/Latino | 116 (25) | 21 (5)
Disease characteristics
UAS7 ≥28, n (%) | 298 (65) | 269 (60)
Mean HSS7 score | 16 | 16
Mean ISS7 score | 15 | 14
Previous experience of Angioedema, n (%) | 240 (52) | 208 (46)
Previous exposure to anti-IgE biologics, n (%) | 147 (32) | 138 (31)
CSU: chronic spontaneous urticaria, UAS7: weekly urticaria activity score, HSS7: weekly hive severity score, ISS7 score: weekly itch severity score

The reported mean duration of CSU at enrollment across treatment groups was 6.6 and 5.2 years in REMIX-1 and REMIX-2, respectively, with 39% and 29% of the patients having a duration of CSU > 5 years.

The co-primary endpoints were absolute change from baseline in ISS7 and HSS7 at Week 12. The ISS7 (range 0 to 21) was defined as the sum of the daily itch severity scores (range 0 to 3) recorded over a 7-day period. The HSS7 (range 0 to 21) was defined as the sum of the daily hive severity scores (range 0 to 3) recorded over a 7-day period. The key secondary endpoint was absolute change from baseline in UAS7 at Week 12. The UAS7 (range 0 to 42) was a composite of the ISS7 and HSS7.

Secondary endpoints included proportion of patients who achieved UAS7 ≤6 at Weeks 2 and 12, and the proportion of patients who achieved complete absence of itch and hives (UAS7 = 0) at Week 12. In both REMIX-1 and REMIX-2 studies, the co-primary and all secondary endpoints showed statistically significant improvement in itch and hives symptoms in patients treated with RHAPSIDO compared to patients treated with placebo. Results are presented in Table 3.

Table 3 Efficacy Results of Adult Patients with CSU in REMIX-1 and REMIX-2 at Week 12a
 | REMIX-1 |  | REMIX-2
 | RHAPSIDO (N = 309) | Placebo (N = 153) | RHAPSIDO (N = 297) | Placebo (N = 153)
Change from Baseline in ISS7 at Week 12
LS mean (SE) CFB | -9.52 (0.34) | -6.89 (0.47) | -8.95 (0.34) | -5.72 (0.45)
Difference in LS mean (SE) vs placebo | -2.63 (0.54) |  | -3.23 (0.55)
95% CI for difference | -3.70, -1.56 |  | -4.29, -2.16
Change from Baseline in HSS7 at Week 12
LS mean (SE) CFB | -10.47 (0.40) | -6.86 (0.55) | -10.47 (0.39) | -6.00 (0.53)
Difference in LS mean (SE) vs placebo | -3.61 (0.64) |  | -4.47 (0.64)
95% CI for difference | -4.85, -2.36 |  | -5.71, -3.23
Change from Baseline in UAS7 at Week 12
LS mean (SE) CFB | -20.02 (0.72) | -13.79 (0.98) | -19.41 (0.70) | -11.73 (0.95)
Difference in LS mean (SE) vs placebo | -6.22 (1.14) |  | -7.68 (1.14)
95% CI for difference | -8.45, -4.00 |  | -9.91, -5.46
Proportion of Patients with UAS7 ≤6 at Week 2
n (%) | 104 (33.7) | 5 (3.3) | 89 (30.0) | 9 (5.9)
Treatment difference | 30.20 |  | 24.55
(95% CI) | 24.30, 36.10 |  | 18.31, 30.80
Proportion of Patients with UAS7 ≤6 at Week 12
n (%) | 154 (49.8) | 38 (24.8) | 139 (46.8) | 30 (19.6)
Treatment difference | 25.44 |  | 27.61
(95% CI) | 16.48, 34.39 |  | 19.14, 36.08
Proportion of Patients with UAS7 = 0 at Week 12
n (%) | 96 (31.1) | 16 (10.5) | 83 (27.9) | 10 (6.5)
Treatment difference | 20.55 |  | 21.60
(95% CI) | 13.35, 27.75 |  | 15.10, 28.10
LS Mean: Least squares mean, SE: standard error, CFB: change from baseline, CI: confidence interval
a Multiple imputation techniques were implemented for missing data.

Figure 1 shows the effect of RHAPSIDO over time up to Week 24 in REMIX-2 patients treated with RHAPSIDO. The results were similar in REMIX-1.

Figure 1 Mean Change from Baseline in Weekly Itch Severity Score (ISS7) and Hive Severity Score (HSS7) up to Week 24 in REMIX-2 (Observed Data)

Improvements in ISS7 and HSS7 at Week 12 were consistent regardless of patients’ baseline total IgE level.

16 HOW SUPPLIED/STORAGE AND HANDLING

RHAPSIDO tablets are supplied as described in Table 4:

Table 4 RHAPSIDO Tablets and Package Configuration
Strength | Tablet Description | Package Configuration | NDC
25 mg | light yellow, round, curved, unscored, film-coated tablet, debossed with “LV” on one side and Novartis logo on the other side. Tablet diameter is 7 mm. | 40 mL HDPE bottle containing 60 tablets with 2 gm silica gel and a child-resistant closure | 0078-1483-20

Storage

Store at 20°C to 25°C (68°F to 77°F); excursions permitted between 15°C to 30°C (59°F to 86°F) [see USP Controlled Room Temperature]. Dispense and store in the original container in order to protect from moisture.

17 PATIENT COUNSELING INFORMATION

Advise patients to read the FDA-approved patient labeling (Patient Information).

Administration Instructions:

Inform patients to take RHAPSIDO with or without food. Advise patients not to split, crush, or chew the tablet and to swallow the tablet whole with water [see Dosage and Administration (2.1)].

Risk of Bleeding:

Inform patients that bleeding can occur with the use of RHAPSIDO, and to report any signs and symptoms to their healthcare practitioner. Inform patients that RHAPSIDO should be interrupted for 3 to 7 days for any surgical procedures. Instruct patients to inform their healthcare practitioner if they use RHAPSIDO with antithrombotic agents due to the potential increased risk of bleeding [see Dosage and Administration (2.2) and Warnings and Precautions (5.1)].

Live Attenuated Vaccines:

Instruct patients to inform the healthcare practitioner that they are taking RHAPSIDO prior to any potential vaccinations. Advise patients that the vaccines containing live virus (live and live-attenuated) should not be given during treatment with RHAPSIDO [see Warnings and Precautions (5.2)].

Pregnancy:

Advise patients that there is a pregnancy registry that monitors pregnancy outcomes in women exposed to RHAPSIDO during pregnancy [see Use in Specific Populations (8.1)].

Distributed by:
Novartis Pharmaceuticals Corporation
One Health Plaza
East Hanover, New Jersey 07936

© Novartis

T2025-55

Patient Information
RHAPSIDO® (RAP-si-doe)
(remibrutinib)
tablets, for oral use

What is RHAPSIDO?
RHAPSIDO is a prescription medicine used to treat adults with chronic spontaneous urticaria (CSU) who continue to have symptoms that are not controlled with antihistamine treatment.
RHAPSIDO should not be used to treat any other forms of hives (urticaria).
It is not known if RHAPSIDO is safe and effective in children.

Before taking RHAPSIDO, tell your healthcare provider about all of your medical conditions, including if you:

- have had a recent surgery or plan to have surgery. Your healthcare provider may tell you to stop taking RHAPSIDO for at least 3 to 7 days before and after any planned medical or surgical procedures.
- have bleeding problems or are taking a blood thinner medicine.
- have liver problems.
- are pregnant or plan to become pregnant. It is not known if RHAPSIDO will harm your unborn baby.
  Pregnancy Exposure Registry: If you become pregnant during treatment with RHAPSIDO, talk to your healthcare provider about registering in the pregnancy exposure registry for RHAPSIDO. You or your healthcare provider can enroll in this registry by calling 1-888-669-6682. The purpose of this registry is to collect information about the safety of RHAPSIDO during pregnancy.
- are breastfeeding or plan to breastfeed. It is not known if RHAPSIDO passes into your breast milk. You and your healthcare provider should decide the best way to feed your baby while taking RHAPSIDO.
- have recently received or are scheduled to receive an immunization (vaccine). Talk to your healthcare provider about receiving any immunizations before taking RHAPSIDO. You should not receive live or live-attenuated vaccines during treatment with RHAPSIDO.

Tell your healthcare provider about all the medicines you take, including prescription and over-the-counter medicines, vitamins, and herbal supplements. Taking RHAPSIDO with certain other medicines may affect how RHAPSIDO works, or it may affect how other medicines work and can cause side effects.

How should I take RHAPSIDO?

- Take RHAPSIDO exactly as your healthcare provider tells you to take it.
- Do not change your dose or stop taking RHAPSIDO unless your healthcare provider tells you to.
- Take 1 RHAPSIDO tablet 2 times a day.
- RHAPSIDO can be taken with or without food.
- Swallow RHAPSIDO tablet whole with water. Do not split, crush, or chew the tablets.
- If you miss a dose of RHAPSIDO, skip the missed dose, and take the next dose at your regular time. Do not take an extra dose of RHAPSIDO to make up for a missed dose.
- If you take too much RHAPSIDO, call your healthcare provider or Poison Help line at 1-800-222-1222, or go to the nearest hospital emergency room right away.

What are possible side effects of RHAPSIDO?
RHAPSIDO may cause serious side effects, including:
Risk of bleeding. Bleeding may happen while being treated with RHAPSIDO. Your healthcare provider will monitor you for signs and symptoms of bleeding and may stop your treatment if bleeding happens. Your risk of bleeding may increase if you are also taking a blood thinner medicine. Tell your healthcare provider right away if you get any signs or symptoms of bleeding, such as:

- bruising, or red or purple skin marks
- pink or brown urine
- headache, dizziness, confusion, or feeling weak
- red or black stools that look like tar

The most common side effects with RHAPSIDO may include nasal congestion, sore throat, and runny nose (nasopharyngitis), bleeding, headache, nausea, abdominal pain.
These are not all the possible side effects of RHAPSIDO.
Call your doctor for medical advice about side effects. You may report side effects to FDA at 1-800-FDA-1088.

How should I store RHAPSIDO?

- Store RHAPSIDO at room temperature between 68°F to 77°F (20°C to 25°C).
- Store RHAPSIDO in the original container to protect from moisture.

Keep RHAPSIDO and all medicines out of the reach of children.

General information about the safe and effective use of RHAPSIDO.
Medicines are sometimes prescribed for purposes other than those listed in a Patient Information leaflet. Do not use RHAPSIDO for a condition for which it is not prescribed. Do not give RHAPSIDO to other people, even if they have the same symptoms that you have. It may harm them. You can ask your healthcare provider or pharmacist for information about RHAPSIDO that is written for health professionals.

What are the ingredients in RHAPSIDO?

- Active Ingredient: remibrutinib
- Inactive Ingredients: copovidone, croscarmellose sodium, mannitol, microcrystalline cellulose, sodium lauryl sulfate, and sodium stearyl fumarate. The tablet coating is composed of polyethylene glycol 4000, polyvinyl alcohol, red iron oxide (E172), talc, titanium dioxide (E171), and yellow iron oxide (E172).

Distributed by:
Novartis Pharmaceuticals Corporation, One Health Plaza, East Hanover, NJ 07936
For more information, go to www.RHAPSIDO.com or call 1-888-669-6682.

This Patient Information has been approved by the U.S. Food and Drug Administration

Issued: 9/2025

© Novartis

T2025-56

PRINCIPAL DISPLAY PANEL

NDC 0078-1483-20

Rhapsido®

(remibrutinib) tablets

25 mg per tablet

Swallow tablets whole with water.

Do not split, crush, or chew tablets.

Rx only

60 tablets

NOVARTIS